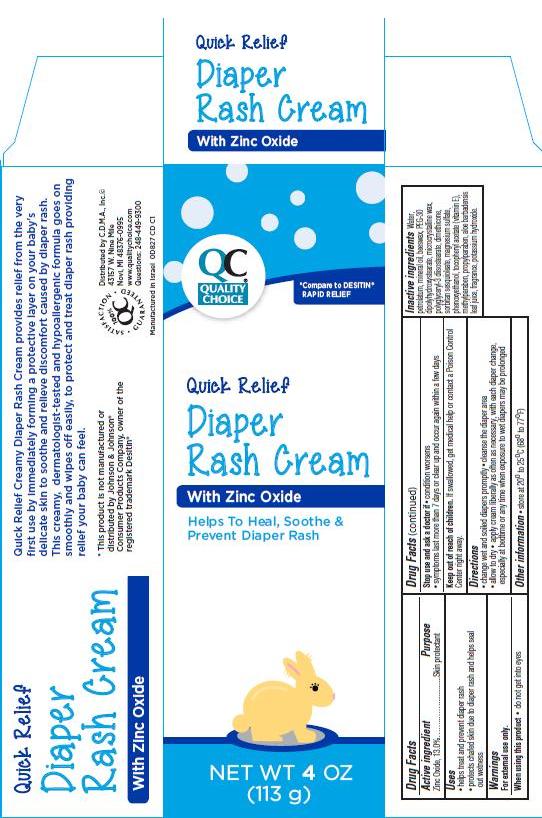 DRUG LABEL: Quality Choice Quick Relief Diaper Rash
NDC: 63868-164 | Form: CREAM
Manufacturer: Chain Drug Marketing Association
Category: otc | Type: HUMAN OTC DRUG LABEL
Date: 20140408

ACTIVE INGREDIENTS: ZINC OXIDE 13 g/100 g
INACTIVE INGREDIENTS: WATER; PETROLATUM; MINERAL OIL; ROYAL JELLY; PEG-30 DIPOLYHYDROXYSTEARATE; MICROCRYSTALLINE WAX; POLYGLYCERYL-3 DIISOSTEARATE; DIMETHICONE; SORBITAN SESQUIOLEATE; MAGNESIUM SULFATE; PHENOXYETHANOL; .ALPHA.-TOCOPHEROL ACETATE; METHYLPARABEN; PROPYLPARABEN; ALOE VERA LEAF; POTASSIUM HYDROXIDE

Quick Relief Diaper Rash Cream

Active ingredient

Zinc Oxide, 13.0%

Purpose

Skin protectant

Uses

- helps treat and prevent diaper rash
- protects chafed skin due to diaper rash and helps seal out wetness

Warnings

For external use only.

When using this product

- do not get into eyes

Stop use and ask a doctor if

- condition worsens
- symptoms last more than 7 days or clear up and occur again within a few days

Keep Out of Reach of Children.

If swallowed, get medical help or contact a Poison Control Center right away.

Directions

- change wet and soiled diapers promptly
- cleanse the diaper area
- allow to dry
- apply cream liberally as often as necessary, with each diaper change, especially at bedtime or any time when exposure to wet diapers may be prolonged

Other Information

- store at 20° to 25°C (68° to 77°F)

Inactive ingredients

water, petrolatum, mineral oil, beeswax, PEG-30 dipolyhydroxystearate, microcrystalline wax, polyglyceryl-3 diisostearate, dimethicone, sorbitan sesquioleate, magnesium sulfate, phenoxyethanol, tocopheryl acetate (vitamin E), methylparaben, propylparaben, aloe barbadensis leaf juice, fragrance, potassium hydroxide.

Package/Label Principal Display Panel

Quick Relief Diaper Rash Cream
with Zinc Oxide

Helps To Heal, Soothe & Prevent Diaper Rash

NET WT 4 OZ. (113 g)

*Compare to DESITIN® RAPID RELIEF

Quick Relief Creamy Diaper Rash Cream provides relief from the very first use by immediately forming a protective layer on your baby’s delicate skin to soothe and relieve discomfort caused by diaper rash. This creamy, dermatologist-tested and hypoallergenic formula goes on smoothly and wipes off easily, to protect and treat diaper rash providing relief your baby can feel.

*This product is not manufactured or distributed by Johnson & Johnson®
Consumer Products Company, owner of the registered trademark Desitin®

Distributed by C.D.M.A., Inc.©
43157 W. Nine Mile
Novi, MI 48376-0995
www.qualitychoice.com
Questions: 248-449-9300

Manufactured in Israel
0D827 CD C1

SATISFACTION GUARANTEED

Carton Label